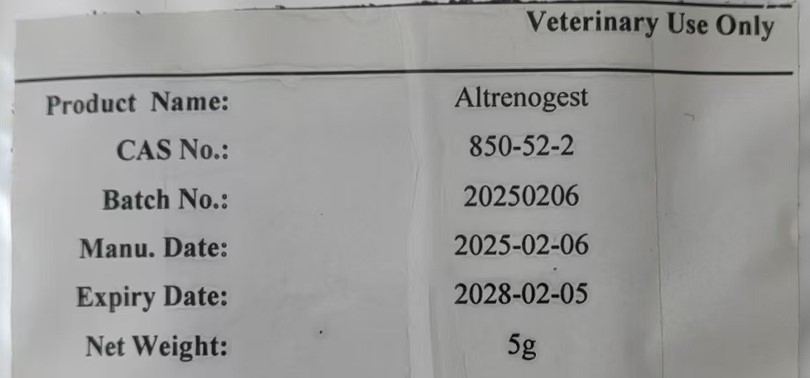 DRUG LABEL: Altrenogest
NDC: 86231-001 | Form: POWDER
Manufacturer: Hangzhou Yumei Biotechnology Co.,Ltd
Category: other | Type: BULK INGREDIENT - ANIMAL DRUG
Date: 20250728

ACTIVE INGREDIENTS: ALTRENOGEST 1 kg/1 kg

Altrenogest